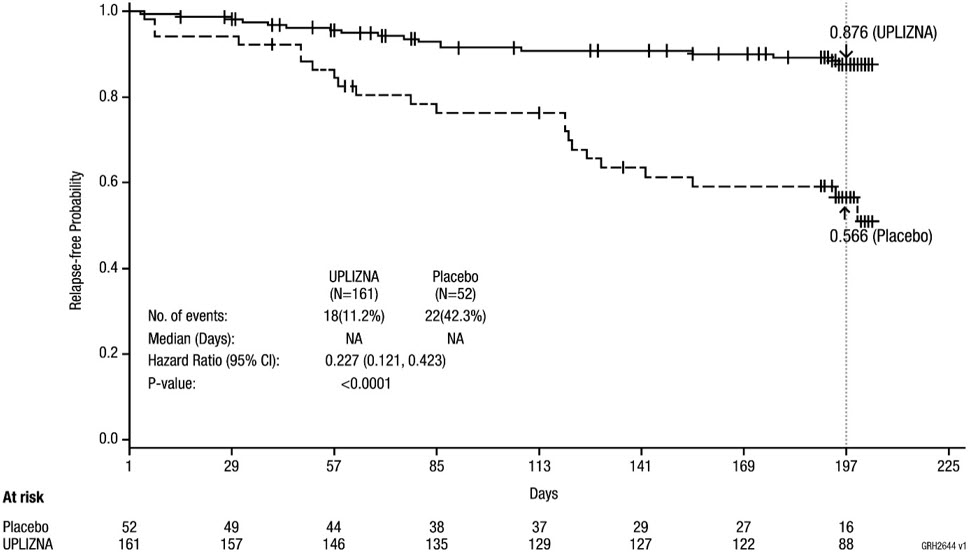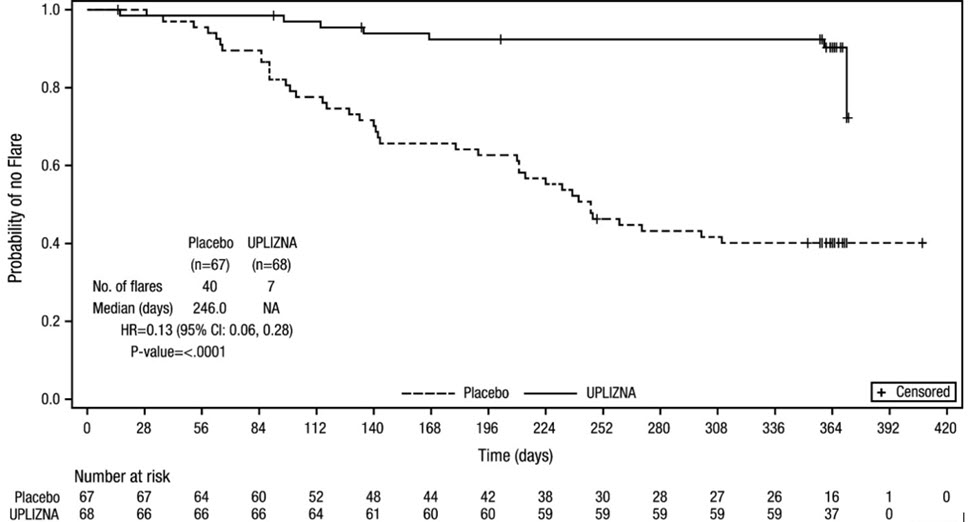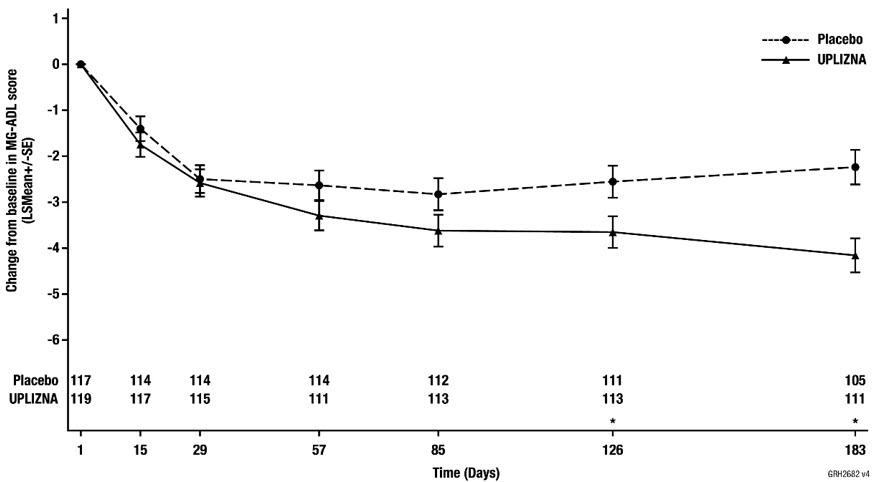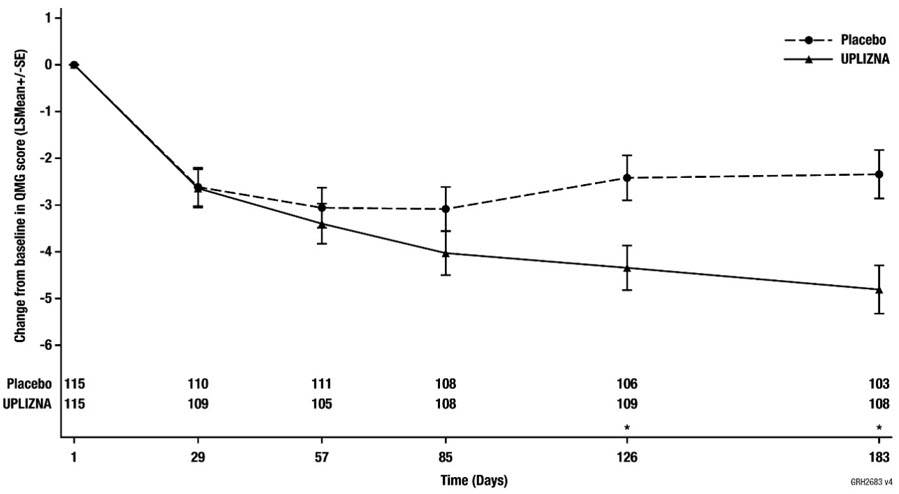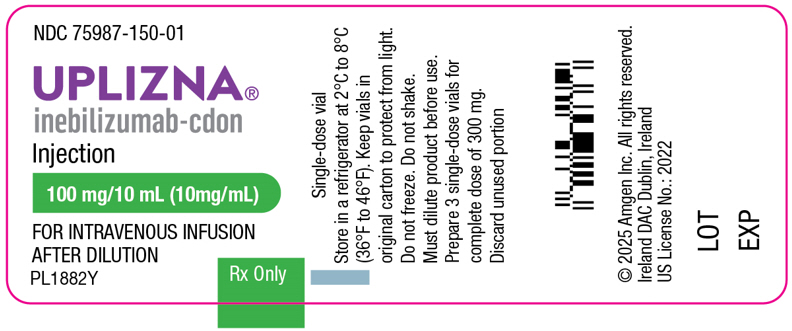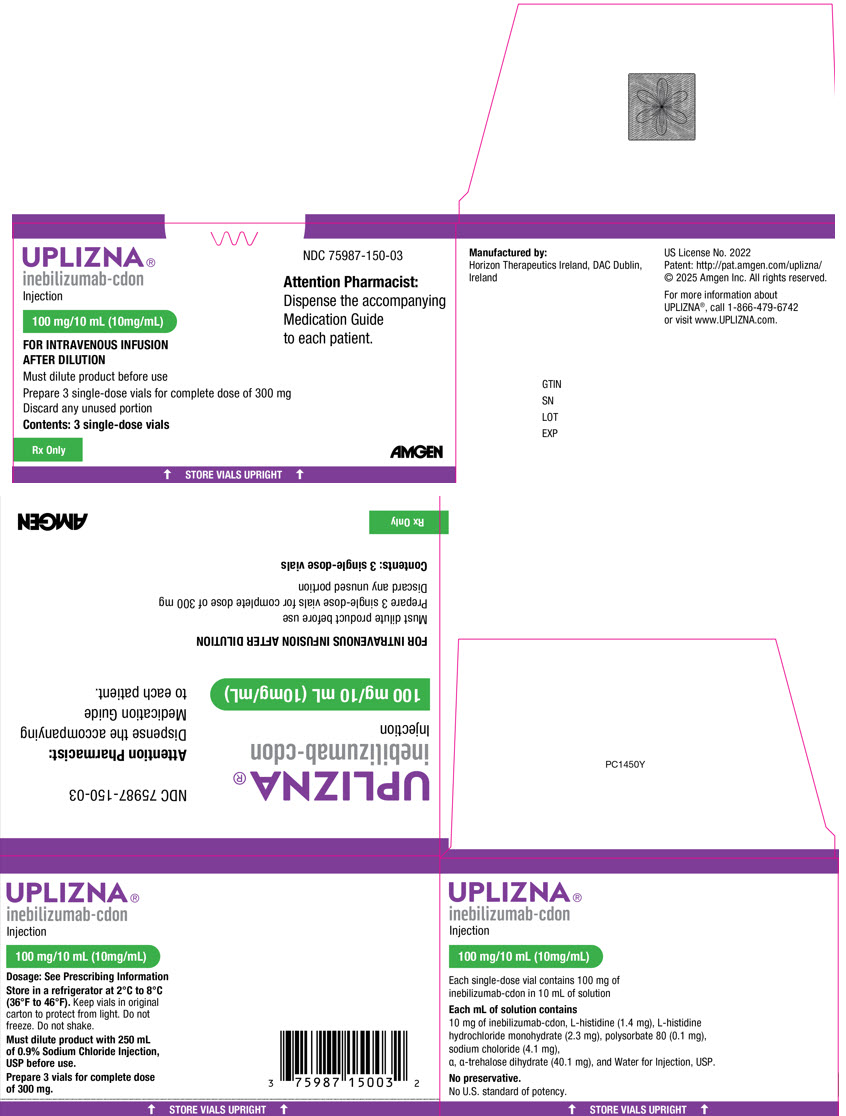 DRUG LABEL: UPLIZNA
NDC: 75987-150 | Form: INJECTION
Manufacturer: Horizon Therapeutics USA, Inc.
Category: prescription | Type: HUMAN PRESCRIPTION DRUG LABEL
Date: 20251211

ACTIVE INGREDIENTS: INEBILIZUMAB 10 mg/1 mL
INACTIVE INGREDIENTS: HISTIDINE 1.4 mg/1 mL; HISTIDINE HYDROCHLORIDE MONOHYDRATE 2.3 mg/1 mL; TREHALOSE DIHYDRATE 40.1 mg/1 mL; SODIUM CHLORIDE 4.1 mg/1 mL; POLYSORBATE 80 0.1 mg/1 mL; WATER

HIGHLIGHTS OF PRESCRIBING INFORMATION

These highlights do not include all the information needed to use UPLIZNA® safely and effectively. See full prescribing information for UPLIZNA®.
UPLIZNA® (inebilizumab-cdon) injection, for intravenous use
Initial U.S. Approval: 2020

RECENT MAJOR CHANGES

Indications and Usage (1.2, 1.3) | 12/2025
Dosage and Administration (2.3) | 12/2025
Warnings and Precautions (5.1, 5.2) | 12/2025

1 INDICATIONS AND USAGE

UPLIZNA is a CD19-directed cytolytic antibody indicated for the treatment of:

- Neuromyelitis optica spectrum disorder (NMOSD) in adult patients who are anti-aquaporin-4 (AQP4) antibody positive. (1.1)
- Immunoglobulin G4-related disease (IgG4-RD) in adult patients. (1.2)
- Generalized myasthenia gravis (gMG) in adult patients who are anti-acetylcholine receptor (AChR) or anti-muscle specific tyrosine kinase (MuSK) antibody positive. (1.2)

2 DOSAGE AND ADMINISTRATION

- Hepatitis B virus, quantitative serum immunoglobulins, and tuberculosis screening is required before the first dose. (2.1)
- Prior to every infusion:
  - Determine if there is an active infection (2.2, 5.2)
  - Premedicate with a corticosteroid, an antihistamine, and an antipyretic (2.2, 5.1)
- UPLIZNA must be diluted in 250 mL of 0.9% Sodium Chloride Injection, USP prior to administration. (2.3, 2.4)
- UPLIZNA is administered as an intravenous infusion titrated to completion, approximately 90 minutes. The recommended dose is:
  - Initial dose: 300 mg intravenous infusion followed two weeks later by a second 300 mg intravenous infusion.
  - Subsequent doses (starting 6 months from the first infusion): single 300 mg intravenous infusion every 6 months. (2.3)
- Monitor patients closely during the infusion and for at least one hour after completion of the infusion. (2.3)

3 DOSAGE FORMS AND STRENGTHS

- Injection: 100 mg/10 mL (10 mg/mL) solution in a single-dose vial (3)

4 CONTRAINDICATIONS

- Previous life-threatening reaction to infusion of UPLIZNA (4)
- Active hepatitis B infection (4)
- Active or untreated latent tuberculosis (4)

5 WARNINGS AND PRECAUTIONS

- Infusion reactions: Administer premedications prior to infusion. (2.2) Management recommendations for infusion reactions depend on the type and severity of the reaction. Permanently discontinue UPLIZNA if a life-threatening or disabling infusion reaction occurs. (5.1)
- Infections: Serious, including life-threatening and fatal infections, have occurred in patients treated with B-cell depleting therapies, including UPLIZNA. Delay UPLIZNA administration in patients with an active infection until the infection is resolved. Vaccination with live-attenuated or live vaccines is not recommended during treatment and after discontinuation, until B-cell repletion. (5.2)
- Immunoglobulin levels: Monitor the level of immunoglobulins at the beginning, during, and after discontinuation of treatment with UPLIZNA until B-cell repletion. Consider discontinuing UPLIZNA if a patient develops a serious opportunistic infection or recurrent infections if immunoglobulin levels indicate immune compromise. (5.3)
- Fetal Risk: May cause fetal harm based on animal data. Advise females of reproductive potential of the potential risk to a fetus and to use an effective method of contraception during treatment and for 6 months after stopping UPLIZNA. (5.4, 8.1)

6 ADVERSE REACTIONS

- The most common adverse reactions (at least 10% of patients treated with UPLIZNA and greater than placebo) were
  - NMOSD: urinary tract infection and arthralgia. (6.1)
  - IgG4-RD: urinary tract infections and lymphopenia. (6.1)
  - gMG: headache and infusion-related reactions. (6.1)

To report SUSPECTED ADVERSE REACTIONS, contact Amgen Inc. at 1-800-77-AMGEN (1-800-772-6436) or FDA at 1-800-FDA-1088 or www.fda.gov/medwatch.

FULL PRESCRIBING INFORMATION

1 INDICATIONS AND USAGE

1.1 Neuromyelitis Optica Spectrum Disorder (NMOSD)

UPLIZNA is indicated for the treatment of neuromyelitis optica spectrum disorder (NMOSD) in adult patients who are anti-aquaporin-4 (AQP4) antibody positive.

1.2 Immunoglobulin G4-Related Disease (IgG4-RD)

UPLIZNA is indicated for the treatment of Immunoglobulin G4-related disease (IgG4-RD) in adult patients.

1.3 Generalized Myasthenia Gravis (gMG)

UPLIZNA is indicated for the treatment of generalized myasthenia gravis (gMG) in adult patients who are anti-acetylcholine receptor (AChR) or anti-muscle specific tyrosine kinase (MuSK) antibody positive.

2 DOSAGE AND ADMINISTRATION

2.1 Assessments Prior to First Dose of UPLIZNA

Hepatitis B Virus Screening

Prior to initiating UPLIZNA, perform Hepatitis B virus (HBV) screening. UPLIZNA is contraindicated in patients with active HBV confirmed by positive results for surface antigen [HBsAg] and anti-HBV tests. For patients who are negative for HBsAg and positive for HB core antibody [HBcAb+] or are carriers of HBV [HBsAg+], consult liver disease experts before starting and during treatment with UPLIZNA [see Contraindications (4) and Warnings and Precautions (5.2)].

Serum Immunoglobulins

Prior to initiating UPLIZNA, perform testing for quantitative serum immunoglobulins. For patients with low serum immunoglobulins, consult immunology experts before initiating treatment with UPLIZNA [see Warnings and Precautions (5.3)].

Tuberculosis Screening

Prior to initiating UPLIZNA, evaluate for active tuberculosis and test for latent infection. For patients with active tuberculosis or positive tuberculosis screening without a history of appropriate treatment, consult infectious disease experts before initiating treatment with UPLIZNA [see Contraindications (4) and Warnings and Precautions (5.2)].

Vaccinations

Because vaccination with live-attenuated or live vaccines is not recommended during treatment and after discontinuation until B-cell repletion, administer all immunizations according to immunization guidelines at least 4 weeks prior to initiation of UPLIZNA for live or live-attenuated vaccines [see Warnings and Precautions (5.2) and Clinical Pharmacology (12.2)].

2.2 Assessment and Premedication Before Every Infusion

Infection Assessment

Prior to every infusion of UPLIZNA, determine whether there is an active infection. In case of active infection, delay infusion of UPLIZNA until the infection resolves [see Warnings and Precautions (5.2)].

Premedication

Table 1 shows premedication to administer prior to each infusion of UPLIZNA to reduce the frequency and severity of infusion reactions [see Warnings and Precautions (5.1)].

Table 1. Premedication Prior to Each UPLIZNA Infusion
Type of Premedication | Route of Administration | Examples (or Equivalent) | Administration Time Prior to UPLIZNA Infusion
corticosteroid | intravenous | methylprednisolone 80 mg to 125 mg | 30 minutes
antihistamine | oral | diphenhydramine 25 mg to 50 mg | 30 to 60 minutes
antipyretic | oral | acetaminophen 500 mg to 650 mg | 30 to 60 minutes

2.3 Recommended Dosage and Administration

NMOSD, IgG4-RD, and gMG

UPLIZNA is administered as an intravenous infusion (see Table 2). The recommended dosage is:

- Initial dose: 300 mg intravenous infusion followed 2 weeks later by a second 300 mg intravenous infusion.
- Subsequent doses (starting 6 months from the first infusion): single 300 mg intravenous infusion every 6 months.

Administration

UPLIZNA must be diluted prior to administration [see Dosage and Administration (2.4)].

Prior to the start of the intravenous infusion, the prepared infusion solution should be at room temperature.

Administer UPLIZNA under the close supervision of an experienced healthcare professional with access to appropriate medical support to manage potential severe reactions such as serious infusion reactions [see Warnings and Precautions (5.1)].

Administer the prepared solution intravenously via an infusion pump at an increasing rate to completion, approximately 90 minutes, according to the schedule in Table 2. Administer through an intravenous line containing a sterile, low-protein binding 0.2 or 0.22 micron in-line filter.

Table 2. Recommended Infusion Rate for UPLIZNA Administration When Diluted in a 250 mL Intravenous Bag
Elapsed Time (minutes) | Infusion Rate (mL/hour)
0-30 | 42
31-60 | 125
61 to completion | 333

Monitor the patient closely for infusion reactions during and for at least one hour after the completion of the infusion.

2.4 Preparation and Storage of Infusion Solution

Preparation

Visually inspect UPLIZNA solution for particulate matter and discoloration [see Dosage Forms and Strengths (3)]. If the solution is cloudy, discolored, or it contains discrete particulate matter, do not use and contact the manufacturer (1-800-772-6436). Do not shake the vial.

Obtain an intravenous bag containing 250 mL of 0.9% Sodium Chloride Injection, USP. Do not use other diluents to dilute UPLIZNA.

Withdraw 10 mL of UPLIZNA from each of the 3 vials contained in the carton and transfer a total of 30 mL into the 250 mL intravenous bag. Mix diluted solution by gentle inversion. Do not shake the solution.

Discard the unused portion remaining in the vials.

Storage of Infusion Solution

UPLIZNA does not contain a preservative.

Administer the prepared infusion solution immediately. If not administered immediately, store the infusion solution for a maximum of 24 hours in the refrigerator between 2°C to 8°C (36°F to 46°F) or 4 hours at room temperature between 20°C to 25°C (68°F to 77°F) prior to the start of the infusion.

3 DOSAGE FORMS AND STRENGTHS

Injection: 100 mg/10 mL (10 mg/mL) clear to slightly opalescent, colorless to slightly yellow solution in a single-dose vial.

4 CONTRAINDICATIONS

UPLIZNA is contraindicated in patients with:

- A history of a life-threatening infusion reaction to UPLIZNA [see Warnings and Precautions (5.1)]
- Active hepatitis B infection [see Warnings and Precautions (5.2)]
- Active or untreated latent tuberculosis [see Warnings and Precautions (5.2)]

5 WARNINGS AND PRECAUTIONS

5.1 Infusion Reactions

UPLIZNA can cause infusion reactions, including anaphylaxis. Symptoms of infusion reactions can include headache, nausea, somnolence, dyspnea, fever, myalgia, rash, or palpitations. Infusion reactions were observed in 9.3%, 7.4%, and 10.1% of patients treated with UPLIZNA during the randomized controlled periods of Study 1 in patients with NMOSD, Study 2 in patients with IgG4-RD, and Study 3 in patients with gMG, respectively. Infusion reactions were most common with the first infusion but were also observed during subsequent infusions.

Reducing the Risk of Infusion Reactions and Managing Infusion Reactions

Administer pre-medication with a corticosteroid, an antihistamine, and an antipyretic [see Dosage and Administration (2.2)].

Management recommendations for infusion reactions depend on the type and severity of the reaction. For life-threatening infusion reactions, immediately and permanently stop UPLIZNA and administer appropriate supportive treatment. For less severe infusion reactions, management may involve temporarily stopping the infusion, reducing the infusion rate, and/or administering symptomatic treatment.

5.2 Infections

Serious, including life-threatening or fatal, bacterial, fungal, and new or reactivated viral infections have been observed during and following completion of treatment with B-cell depleting therapies, including UPLIZNA.

The most common infections reported by UPLIZNA-treated patients in the randomized and open-label clinical trial periods for NMOSD included urinary tract infection (20%), nasopharyngitis (13%), upper respiratory tract infection (8%), and influenza (7%). In the IgG4-RD randomized controlled and open-label periods, the most common infections reported by UPLIZNA-treated patients were upper respiratory tract infection (11%), nasopharyngitis (10%), urinary tract infection (9%), and influenza (6%). In the gMG randomized controlled period, the most common infections reported by UPLIZNA-treated patients were urinary tract infection (7%) and nasopharyngitis (7%).

Delay UPLIZNA administration in patients with an active infection until the infection is resolved.

Possible Increased Risk of Immunosuppressant Effects with Other Immunosuppressants

If combining UPLIZNA with another immunosuppressive therapy, consider the potential for increased immunosuppressive effects.

Hepatitis B Virus (HBV) Reactivation

HBV reactivation has been observed with the use of B-cell depleting therapies, including UPLIZNA. Fulminant hepatitis, hepatic failure, and death caused by HBV reactivation have occurred in patients treated with B-cell depleting therapies.

HBV reactivation was observed in a patient treated with UPLIZNA during the gMG clinical trial, and has also been observed in the postmarketing setting. Patients with active or chronic HBV infection were excluded from clinical trials.

Perform HBV screening in all patients before initiation of treatment with UPLIZNA. Do not administer UPLIZNA to patients with active HBV infection confirmed by positive results for HBsAg and anti-HB tests. For patients who are negative for HBsAg and positive for HBcAb, or who are carriers of HBV (i.e., HBsAg+), consult liver disease experts before starting and during treatment with UPLIZNA.

Progressive Multifocal Leukoencephalopathy (PML)

PML is an opportunistic viral infection of the brain caused by the JC virus that typically only occurs in patients who are immunocompromised, and that usually leads to death or severe disability. Although no confirmed cases of PML were identified in UPLIZNA clinical trials, JC virus infection resulting in PML has been observed in patients treated with other B-cell depleting antibodies and other therapies that affect immune competence. In UPLIZNA clinical trials one subject died following the development of new brain lesions for which a definitive diagnosis could not be established, though the differential diagnosis included an atypical NMOSD relapse, PML, or acute disseminated encephalomyelitis. At the first sign or symptom suggestive of PML, withhold UPLIZNA and perform an appropriate diagnostic evaluation. MRI findings may be apparent before clinical signs or symptoms. Typical symptoms associated with PML are diverse, progress over days to weeks, and include progressive weakness on one side of the body or clumsiness of limbs, disturbance of vision, and changes in thinking, memory, and orientation leading to confusion and personality changes.

Tuberculosis

Patients should be evaluated for tuberculosis risk factors and tested for latent infection prior to initiating UPLIZNA. Consider anti-tuberculosis therapy prior to initiation of UPLIZNA in patients with a history of latent active tuberculosis in whom an adequate course of treatment cannot be confirmed, and for patients with a negative test for latent tuberculosis but having risk factors for tuberculosis infection. Consult infectious disease experts regarding whether initiating anti-tuberculosis therapy is appropriate before starting treatment.

Vaccinations

Administer all immunizations according to immunization guidelines at least 4 weeks prior to initiation of UPLIZNA. The safety of immunization with live or live-attenuated vaccines following UPLIZNA therapy has not been studied, and vaccination with live-attenuated or live vaccines is not recommended during treatment and until B-cell repletion.

Vaccination of Infants Born to Mothers Treated with UPLIZNA During Pregnancy

In infants of mothers exposed to UPLIZNA during pregnancy, do not administer live or live-attenuated vaccines before confirming recovery of B-cell counts in the infant. Depletion of B-cells in these exposed infants may increase the risks from live or live-attenuated vaccines. Non-live vaccines, as indicated, may be administered prior to recovery from B-cell and immunoglobulin level depletion, but consultation with a qualified specialist should be considered to assess whether a protective immune response was mounted [see Use in Specific Populations (8.1)].

5.3 Reduction in Immunoglobulins

There may be a progressive and prolonged hypogammaglobulinemia or decline in the levels of total and individual immunoglobulins such as immunoglobulins G and M (IgG and IgM) with continued UPLIZNA treatment [see Adverse Reactions (6.1)]. Monitor the levels of quantitative serum immunoglobulins during treatment with UPLIZNA, especially in patients with opportunistic or recurrent infections, and until B-cell repletion after discontinuation of therapy. Consider discontinuing UPLIZNA therapy if a patient with low immunoglobulin G or M develops a serious opportunistic infection or recurrent infections, or if prolonged hypogammaglobulinemia requires treatment with intravenous immunoglobulins.

5.4 Fetal Risk

Based on animal data, UPLIZNA can cause fetal harm due to B-cell lymphopenia and reduce antibody response in offspring exposed to UPLIZNA even after B-cell repletion. Transient peripheral B-cell depletion and lymphocytopenia have been reported in infants born to mothers exposed to other B-cell depleting antibodies during pregnancy. Advise females of reproductive potential to use effective contraception while receiving UPLIZNA and for at least 6 months after the last dose [see Use in Specific Populations (8.1)].

6 ADVERSE REACTIONS

The following clinically significant adverse reactions are described elsewhere in the labeling:

- Infusion Reactions [see Warnings and Precautions (5.1)]
- Infections [see Warnings and Precautions (5.2)]
- Reduction in Immunoglobulins [see Warnings and Precautions (5.3)]

6.1 Clinical Trial Experience

Because clinical trials are conducted under widely varying conditions, adverse reaction rates observed in the clinical trials of a drug cannot be directly compared to rates in the clinical trials of another drug and may not reflect the rates observed in practice.

Adverse Reactions

NMOSD

The safety of UPLIZNA was evaluated in Study 1, in which 161 patients were exposed to UPLIZNA at the recommended dosage regimen during the randomized, controlled treatment period; during which 52 patients received placebo [see Dosage and Administration (2.1) and Clinical Studies (14)]. Subsequently, 198 patients were exposed to UPLIZNA during an open-label treatment period.

Two-hundred and eight patients in the randomized and open-label treatment periods had a total of 324 person-years of exposure to UPLIZNA, including 165 patients with exposure for at least 6 months and 128 with exposure for one year or more.

Table 3 lists adverse reactions that occurred in at least 5% of patients treated with UPLIZNA and at a greater incidence than in patients who received placebo in Study 1. The most common adverse reactions (incidence of at least 10% in patients treated with UPLIZNA and at a greater incidence than placebo) were urinary tract infection and arthralgia.

Table 3. Adverse Reactions in Patients with NMOSD with an Incidence of at Least 5% with UPLIZNA and a Greater Incidence than Placebo in Study 1
Adverse Reactions | UPLIZNA N = 161 % | Placebo N = 52 %
Urinary tract infection | 11 | 10
Arthralgia | 10 | 4
Headache | 8 | 8
Back pain | 7 | 4

Across both the randomized and open-label treatment in Study 1, the most common adverse reactions (greater than 10%) were urinary tract infection (20%), nasopharyngitis (13%), infusion reaction (12%), arthralgia (11%), and headache (10%).

IgG4-RD

The safety of UPLIZNA was evaluated in Study 2, in which 68 patients were exposed to UPLIZNA at the recommended dosage regimen during the randomized, controlled treatment period; during which 67 patients received placebo [see Dosage and Administration (2.1) and Clinical Studies (14)].

Table 4 lists adverse reactions that occurred in at least 5% of patients treated with UPLIZNA and at a greater incidence than in patients who received placebo in Study 2. The most common adverse reactions (incidence of at least 10% in patients treated with UPLIZNA and at a greater incidence than placebo) were urinary tract infection and lymphopenia.

Table 4. Adverse Reactions in Patients with IgG4-RD with an Incidence of at Least 5% with UPLIZNA and a Greater Incidence than Placebo in Study 2
Adverse Reactions | UPLIZNA N = 68 % | Placebo N = 67 %
Lymphopenia | 19 [Lymphopenia includes both lymphopenia and lymphocyte count decreased.] | 9
Urinary tract infection | 12 | 6
Pyrexia | 9 | 5
Neutropenia | 6 | 5
Myalgia | 6 | 0

Additional adverse reactions during the randomized controlled period in Study 2 were infusion related reactions, influenza, and pneumonia.

gMG

The safety of UPLIZNA was evaluated in Study 3, in which 119 patients were exposed to UPLIZNA at the recommended dosage regimen and 119 patients received placebo during the randomized, placebo-controlled treatment period. The randomized controlled treatment period was 52 weeks for patients who were anti-AChR antibody positive (n=95 each group) and 26 weeks for patients who were anti-MuSK antibody positive (n=24 each group) [see Dosage and Administration (2.1) and Clinical Studies (14)]. References to adverse reaction frequency in the overall population in the randomized controlled period of Study 3 are reflective of 52-week data for the anti-AChR antibody positive population, and 26-week data for the anti-MuSK antibody positive population that were available at the time of the primary analysis.

Table 5 lists adverse reactions that occurred in at least 5% of patients treated with UPLIZNA and at a greater incidence than in patients who received placebo in Study 3. The most common adverse reactions (incidence of at least 10% in patients treated with UPLIZNA and at a greater incidence than placebo) were headache and infusion-related reaction.

Table 5. Adverse Reactions in Patients with gMG with an Incidence of at Least 5% with UPLIZNA and a Greater Incidence than Placebo in Study 3
Adverse Reactions [Based on the overall randomized controlled period, comprised of 52 weeks for the anti-AChR antibody positive population and 26 weeks for the anti-MuSK antibody positive population] | UPLIZNA N = 119 % | Placebo N = 119 %
Headache | 15 | 7
Infusion-related reaction [Infusion-related reaction was defined as any sign or symptom experienced by patients during the infusion of study drug, or any adverse event occurring within 24 hours of study drug administration for which an alternative explanation was not evident.] | 10 | 6
Nasopharyngitis | 7 | 3
Cough | 7 | 3
Urinary tract infection | 7 | 3

Laboratory Abnormalities

Decreased Immunoglobulins

NMOSD

At the end of the 6.5-month randomized, controlled period, relative to baseline, the total immunoglobulin level was reduced approximately 8% from baseline for patients treated with UPLIZNA as compared to an increase of 6% in patients treated with placebo. The mean decreases from baseline in immunoglobulin G (IgG) and immunoglobulin M (IgM) were approximately 4% and 32%, respectively, in patients treated with UPLIZNA, whereas IgG was increased by 6% and IgM was increased by approximately 13% in placebo-treated patients. The proportion of patients treated with UPLIZNA who had IgG levels below the lower limit of normal at year 1 was 7% and at year 2 was 13%. The proportion of patients treated with UPLIZNA who had IgM levels below the lower limit of normal at year 1 was 31% and at year 2 was 42%.

IgG4-RD

At the end of the 12-month randomized, controlled period, relative to baseline, the total immunoglobulin level was reduced approximately 12% from baseline for patients treated with UPLIZNA as compared to an increase of 21% in patients treated with placebo. The mean decreases from baseline in IgG and IgM were approximately 9% and 32%, respectively, in patients treated with UPLIZNA, whereas IgG was increased by 26% and IgM was increased by approximately 3% in placebo-treated patients.

gMG

At the end of the 26-week randomized, controlled period, relative to baseline, the total immunoglobulin level was reduced approximately 13% from baseline for patients treated with UPLIZNA as compared to an increase of 15% in patients treated with placebo. The mean decreases from baseline in IgG and IgM were approximately 8% and 30%, respectively, in patients treated with UPLIZNA, whereas IgG was increased by 18% and IgM was increased by approximately 5% in placebo-treated patients. The proportion of patients treated with UPLIZNA who had IgG and IgM levels below the lower limit of normal at the end of the 26-week randomized, controlled period was 29% and 16%, respectively, compared to 8% and 4%, respectively, in the placebo group.

Decreased Neutrophil Counts

NMOSD

Neutrophil counts between 1.0-1.5 × 10^9/L were observed in 7% of UPLIZNA-treated patients versus 2% of patients who received placebo. Neutrophil counts between 0.5-1.0 × 10^9/L were observed in 2% of patients treated with UPLIZNA compared to no patients who received placebo. At the end of the 6.5-month randomized, controlled period, the proportion of patients with a neutrophil count below the limit of normal was 12% for patients treated with UPLIZNA compared to 4% for patients who received placebo.

IgG4-RD

During the 12-month randomized, controlled period, neutrophil counts between 1.0-1.5 × 10^9/L were observed in 8% of UPLIZNA-treated patients versus 3% of patients who received placebo. Neutrophil counts between 0.5-1.0 × 10^9/L were observed in 2% of patients treated with placebo compared to no patients who received UPLIZNA.

gMG

During the 26-week randomized, controlled period, neutrophil counts between 1.0-1.5 × 10^9/L were observed in 3% of patients who received placebo compared to no patients who received UPLIZNA. Neutrophil counts between 0.5-1.0 × 10^9/L were observed in 1% of patients treated with UPLIZNA compared to no patients who received placebo.

Decreased Lymphocyte Counts

NMOSD

A reduction in lymphocyte counts was observed more frequently in patients treated with UPLIZNA compared to those who received placebo. At the end of the 6.5-month randomized, controlled period, the proportion of patients with a lymphocyte count below the limit of normal was 5% for patients treated with UPLIZNA compared to 4% for patients who received placebo.

IgG4-RD

A reduction in lymphocyte counts was observed more frequently in patients treated with UPLIZNA compared to those who received placebo. During the 12-month randomized, controlled period, the proportion of patients with a lymphocyte count below the limit of normal was 42% for patients treated with UPLIZNA compared to 36% for patients who received placebo.

gMG

A reduction in lymphocyte counts was observed more frequently in patients treated with UPLIZNA compared to those who received placebo. During the 26-week randomized, controlled period, the proportion of patients with a lymphocyte count below the limit of normal was 35% for patients treated with UPLIZNA compared to 31% for patients who received placebo.

7 DRUG INTERACTIONS

7.1 Immunosuppressive or Immune-Modulating Therapies

Concomitant usage of UPLIZNA with immunosuppressant drugs, including systemic corticosteroids, may increase the risk of infection. Consider the risk of additive immune system effects when co-administering immunosuppressive therapies with UPLIZNA.

8 USE IN SPECIFIC POPULATIONS

8.1 Pregnancy

Pregnancy Exposure Registry

There is a pregnancy exposure registry that monitors pregnancy outcomes in women exposed to UPLIZNA during pregnancy or shortly before conception. Healthcare providers are encouraged to advise their patients to register by contacting the UPLIZNA Pregnancy Registry by calling the coordinating center at 1 (303) 724-4644 or www.upliznapregnancyregistry.com.

Risk Summary

UPLIZNA is a humanized IgG1 monoclonal antibody and immunoglobulins are known to cross the placental barrier. There are no adequate data on the developmental risk associated with the use of UPLIZNA in pregnant women. However, transient peripheral B-cell depletion and lymphocytopenia have been reported in infants born to mothers exposed to other B-cell depleting antibodies during pregnancy. B-cell levels in infants following maternal exposure to UPLIZNA have not been studied in clinical trials. The potential duration of B-cell depletion in such infants, and the impact of B-cell depletion on vaccine safety and effectiveness, is unknown [see Warnings and Precautions (5.2)].

In the U.S. general population, the estimated background risk of major birth defects and miscarriage in clinically recognized pregnancies is 2 to 4% and 15 to 20%, respectively.

Data

Animal Data

Intravenous administration of inebilizumab-cdon (0, 3, or 30 mg/kg/week) to human CD19 transgenic (huCD19 Tg) male and female mice prior to and during mating and continuing in females through gestation day 15 resulted in no adverse effects on embryofetal development; however, there was a marked reduction in B-cells in fetal blood and liver at both doses tested. These results demonstrate that inebilizumab-cdon crosses the placenta and depletes B-cells in the fetus.

Intravenous administration of inebilizumab-cdon (0, 3, or 30 mg/kg) to huCD19 Tg mice every three days throughout organogenesis and lactation resulted in depletion of B-cells and persistent reductions in immune function (even following repletion of B-cells and lasting into adulthood) in offspring at both doses tested. At the end of the lactation period, plasma inebilizumab-cdon levels in offspring were only slightly lower than those in maternal plasma. A no-effect level for immunotoxicity in the offspring was not identified.

8.2 Lactation

Risk Summary

There are no data on the presence of inebilizumab-cdon in human milk, the effects on a breastfed infant, or the effects on milk production. Human IgG is excreted in human milk, and the potential for absorption of UPLIZNA to lead to B-cell depletion in the breastfed infant is unknown. The developmental and health benefits of breastfeeding should be considered along with the mother's clinical need for UPLIZNA and any potential adverse effects on the breastfed infant from UPLIZNA or from the underlying maternal condition.

8.3 Females of Reproductive Potential

Contraception

Women of childbearing potential should use contraception while receiving UPLIZNA and for 6 months after the last infusion of UPLIZNA [see Clinical Pharmacology (12.3)].

8.4 Pediatric Use

Safety and effectiveness in pediatric patients have not been established.

8.5 Geriatric Use

NMOSD

Clinical studies of UPLIZNA did not include sufficient numbers of patients aged 65 and over to determine whether they respond differently from younger patients (aged 18 to 64 years of age).

IgG4-RD

Twenty-nine percent (32 out of 112) of patients 65 years of age or older, were treated with UPLIZNA. There were no overall age-related differences in safety or efficacy observed compared to younger patients (aged 18 to 64 years of age).

gMG

Clinical studies of UPLIZNA did not include sufficient numbers of patients aged 65 and older to determine whether they respond differently from younger patients (aged 18 to 64 years of age).

11 DESCRIPTION

Inebilizumab-cdon is a CD19-directed humanized afucosylated IgG1 monoclonal antibody produced by recombinant DNA technology in Chinese hamster ovary (CHO) cell suspension culture. The molecular weight is approximately 149 kDa.

UPLIZNA (inebilizumab-cdon) injection is a sterile, preservative-free, clear to slightly opalescent, colorless to slightly yellow solution, free from visible particles, for intravenous use.

Each single-dose vial contains 100 mg of inebilizumab in 10 mL of solution. Each mL contains 10 mg of inebilizumab-cdon, L-histidine (1.4 mg), L-histidine hydrochloride monohydrate (2.3 mg), polysorbate 80 (0.1 mg), sodium chloride (4.1 mg), α,α-trehalose dihydrate (40.1 mg), and Water for Injection, USP and a pH of 6.

12 CLINICAL PHARMACOLOGY

12.1 Mechanism of Action

The mechanism by which inebilizumab-cdon exerts its therapeutic effects in NMOSD, IgG4-RD, and gMG is presumed to involve binding to CD19, a cell surface antigen presents on pre-B and mature B lymphocytes. Following cell surface binding to B lymphocytes, inebilizumab-cdon results in antibody-dependent cellular cytolysis.

12.2 Pharmacodynamics

Pharmacodynamics of UPLIZNA were assessed with an assay for CD20+ B-cells, since UPLIZNA can interfere with the CD19+ B-cell assay. Treatment with UPLIZNA reduces CD20+ B-cell counts in blood by 8 days after infusion.

In Study 1 [see Clinical Studies (14.1)], CD20+ B-cell counts were reduced below the lower limit of normal by 4 weeks in 100% of patients treated with UPLIZNA and remained below the lower limit of normal in 94% of patients for 28 weeks after initiation of treatment.

In Study 2 [see Clinical Studies (14.2)], CD20+ B-cell counts were reduced below the lower limit of normal by week 2 in 100% of patients treated with UPLIZNA and remained below the lower limit of normal in 85% of patients for up to 52 weeks after initiation of treatment.

In Study 3 [see Clinical Studies (14.3)], CD20+ B-cell counts were reduced below the lower limit of normal by week 4 in ≥ 99% of patients in the overall population (anti-AChR antibody positive and anti-MuSK antibody positive patients) treated with UPLIZNA. B-cell counts remained below the lower limit of normal in ≥ 96% of patients treated with UPLIZNA in the anti-AChR antibody positive population for 52 weeks after initiation of treatment, and in > 96% of patients treated with UPLIZNA in the anti-MuSK antibody positive population for 26 weeks after initiation of treatment.

12.3 Pharmacokinetics

The pharmacokinetics of inebilizumab-cdon in patients with NMOSD, IgG4-RD, and gMG was similar, and was biphasic with a mean terminal half-life of 18 days.

In patients with NMOSD, the mean maximum concentration was 108 µg/mL (following the second 300 mg dose on day 15), and the cumulative AUC of the 26-week treatment period in which NMOSD patients received two intravenous administrations 2 week apart was 2980 µg∙d/mL.

In patients with IgG4-RD, the mean maximum concentration was 127 µg/mL (following the second 300 mg dose on day 15), and the cumulative AUC of the 52-week treatment period in which IgG4-RD patients received two intravenous administrations 2 weeks apart, followed by a third dose at week 26 was 4290 µg×d/mL.

In patients with gMG, the mean maximum concentration was 139 µg/mL (following the second 300 mg dose on day 15) for the overall population. The cumulative AUC of the 52-week treatment period in which anti-AChR antibody positive patients (n = 84) received two intravenous administrations 2 weeks apart, followed by a third dose at week 26 was 4240 µg×d/mL. The cumulative AUC of the 26-week treatment period in which anti-MuSK antibody positive patients (n = 17) received two intravenous administrations 2 weeks apart was 3740 µg×d/mL.

Distribution

Based on population pharmacokinetic analysis, the estimated typical central and peripheral volume of distribution of inebilizumab-cdon was 2.95 L and 2.57 L, respectively.

Metabolism

Inebilizumab-cdon is a humanized IgG1 monoclonal antibody that is degraded by proteolytic enzymes widely distributed in the body.

Elimination

The results of population pharmacokinetic analysis indicated that the estimated inebilizumab-cdon systemic clearance of the first-order elimination pathway was 0.19 L/day. At low exposure levels, inebilizumab-cdon was likely subject to the receptor (CD19)-mediated clearance, which decreased with time presumably because of the depletion of B-cells by UPLIZNA treatment.

Specific Populations

Gender, Race, Geriatric Use

A population pharmacokinetic analysis indicated that there was no significant effect of gender, race, and age on inebilizumab-cdon clearance.

Renal/Hepatic Impairment

No formal clinical studies have been conducted to investigate the effect of renal impairment or hepatic impairment on inebilizumab-cdon pharmacokinetic parameters.

Drug Interaction Studies

Cytochrome P450 enzymes and transporters are not involved in the clearance of inebilizumab-cdon; therefore, the potential risk of interactions between UPLIZNA and concomitant medications that are substrates, inducers, or inhibitors of cytochrome P450 enzymes and transporters is low.

12.6 Immunogenicity

The observed incidence of anti-drug antibodies is highly dependent on the sensitivity and specificity of the assay. Differences in assay methods preclude meaningful comparisons of the incidence of anti-drug antibodies in the studies described below with the incidence of anti-drug antibodies in other studies, including those of UPLIZNA.

In Study 1, treatment-emergent antibodies (those that appeared or significantly increased from baseline after administration of UPLIZNA), were detected in 5.6% patients receiving UPLIZNA. Although these data do not demonstrate an impact of anti-inebilizumab-cdon antibody development on the efficacy or safety of UPLIZNA in these patients, the available data are too limited to make definitive conclusions.

In Study 2, the incidence of treatment-emergent anti-inebilizumab-cdon antibodies was 8.8% (6/68) of patients receiving UPLIZNA during the 52-week randomized controlled period. Neutralizing antibodies were not directly assessed. There was no identified clinically significant effect of anti--inebilizumab--cdon antibodies on pharmacokinetics, pharmacodynamics, safety or effectiveness of UPLIZNA.

In Study 3, treatment-emergent anti-inebilizumab-cdon antibodies were detected in 0.8% (1/119) of patients receiving UPLIZNA during the randomized controlled period. Neutralizing antibodies were not directly assessed. The available data are too limited to make definitive conclusions regarding the impact of anti-inebilizumab-cdon antibodies on pharmacokinetics, pharmacodynamics, safety, or effectiveness of UPLIZNA.

13 NONCLINICAL TOXICOLOGY

13.1 Carcinogenesis, Mutagenesis, Impairment of Fertility

Carcinogenesis

No studies have been conducted to assess the carcinogenic potential of inebilizumab-cdon.

Mutagenesis

No studies have been conducted to assess the genotoxic potential of inebilizumab-cdon.

Impairment of Fertility

Intravenous administration of inebilizumab-cdon (0, 3, or 30 mg/kg/week) to human CD19 transgenic male and female mice prior to and during mating and continuing in females through gestation day 15 resulted in reduced fertility at both doses tested. A no-effect dose for adverse effects on fertility was not identified.

14 CLINICAL STUDIES

14.1 Neuromyelitis Optica Spectrum Disorder (NMOSD)

The efficacy of UPLIZNA for the treatment of NMOSD was established in Study 1 (NCT02200770), a randomized (3:1), double-blind, placebo-controlled trial that enrolled 213 patients with NMOSD who were anti-AQP4 antibody positive and 17 who were anti-AQP4 antibody negative.

Patients met the following eligibility criteria:

1. A history of one or more relapses that required rescue therapy within the year prior to screening, or 2 or more relapses that required rescue therapy in 2 years prior to screening.
2. Expanded Disability Status Scale (EDSS) score of 7.5 or less. Patients with an EDSS score of 8.0 were eligible if they were deemed capable of participating.
3. Patients were excluded if previously treated with immunosuppressant therapies within an interval specified for each such therapy.

The use of immunosuppressants during the blinded phase of the trial was prohibited.

The use of oral or intravenous corticosteroids during the blinded phase of the trial was prohibited, with the exception of premedication for investigational treatment and treatment for a relapse.

Of the 213 enrolled anti-AQP4 antibody positive patients, a total of 161 were randomized to receive treatment with UPLIZNA, and 52 were randomized to receive placebo.

The baseline demographic and disease characteristics were balanced between the treatment groups. Females accounted for 94% of the study population. Fifty-two percent of patients were White, 21% Asian, and 9% Black or African American. The mean age was 43 years (range 18 to 74 years). The mean EDSS score was 4.0. The number of relapses in the two years prior to randomization was 2 or more in 83% of the patients.

UPLIZNA was administered according to the recommended dosage regimen [see Dosage and Administration (2.4)].

All potential relapses were evaluated by a blinded, independent, adjudication committee, who determined whether the relapse met protocol-defined criteria. Patients who experienced an adjudicated relapse in the randomized-controlled period (RCP), or who completed the Day 197 visit without a relapse, exited the RCP.

The primary efficacy endpoint was the time to the onset of the first adjudicated relapse on or before Day 197.

The time to the first adjudicated relapse was significantly longer in patients treated with UPLIZNA compared to patients who received placebo (relative risk reduction 73%; hazard ratio: 0.272; p < 0.0001). In the anti-AQP4 antibody positive population there was a 77.3% relative reduction (hazard ratio: 0.227, p < 0.0001). There was no evidence of a benefit in patients who were anti-AQP4 antibody negative.

Table 6. Efficacy Results in Study 1 in anti-AQP4 Antibody Positive NMOSD Patients
 | Treatment Group
 | UPLIZNA N = 161 | Placebo N = 52
Time to Adjudication Committee-Determined Relapse (Primary Efficacy Endpoint)
Number (%) of patients with relapse | 18 (11.2%) | 22 (42.3%)
Hazard ratio (95% CI) [Cox regression method, with placebo as the reference group.] | 0.227 (0.121, 0.423)
p-value | < 0.0001

Figure 1. Kaplan-Meier Plot of Time to First Adjudication Committee-Determined NMOSD Relapse in the Randomized-Controlled Period (ITT Population; anti-AQP4 Antibody Positive Patients)

Note: Numbers of patients at risk are shown at each time point.

Compared to placebo-treated patients, patients treated with UPLIZNA who were anti-AQP4 antibody positive had reduced annualized rates of hospitalizations (0.11 for UPLIZNA versus 0.50 for placebo).

14.2 Immunoglobulin G4-Related Disease (IgG4-RD)

The efficacy of UPLIZNA for the treatment of IgG4-RD was established in Study 2 (NCT04540497), a randomized, double-blind, multicenter, 52-week placebo-controlled trial that enrolled 135 adult patients who met the following eligibility criteria:

- Newly diagnosed or recurrent IgG4-RD that required glucocorticoid (GC) treatment at screening.
- Confirmed history of organ involvement at any time in the course of disease.

The concomitant use of biologic and non-biologic immunosuppressive agents was prohibited during the blinded phase of the trial. Of the 135 enrolled IgG4-RD patients, 68 patients were randomized to receive UPLIZNA and 67 were randomized to receive placebo. The baseline demographic and disease characteristics were generally balanced between the treatment groups. Females accounted for 35% of the study population. Thirty-nine percent of patients were White, 47% Asian, and 1% Black or African American. The mean age was 58 years (range 24 to 80 years). The median disease duration was 0.9 years. Forty-six percent of patients were newly diagnosed with IgG4-RD and 54% had recurrent disease.

Patients were at a uniform 20 mg per day dose of glucocorticoids at the time of randomization and then began a prespecified taper of 5 mg dose every two weeks until discontinuation at the end of 8 weeks. The use of glucocorticoids during the trial was permitted for premedication for investigational treatment, treatment for a relapse and in certain situations other than an IgG4-RD flare. UPLIZNA was administered according to the recommended dosage regimen [see Dosage and Administration (2.4)].

Disease flare was defined as new/worsening signs or symptoms that were positively adjudicated and warranted treatment by the investigator. All potential flares were assessed by the investigator and subsequently reviewed by a blinded, independent, adjudication committee, who determined whether the flare met one or more of the protocol-defined, organ-specific flare diagnostic criteria.

The primary efficacy endpoint was the time to First Treated and Adjudication Committee (AC)-determined IgG4-RD flare within the 52-week RCP. The time to the First Treated and AC determined IgG4-RD flare was significantly longer in the UPLIZNA group, compared with the placebo group (Figure 2). UPLIZNA reduced the risk of treated and AC-determined IgG4-RD flare by 87%, compared with placebo (hazard ratio: 0.13; p < 0.0001) (see Table 6).

Figure 2. Kaplan-Meier Plot of Time to First Treated and Adjudication Committee-Determined IgG4-RD Flare During the Randomized-Controlled Period

Patients who did not complete the RCP and who did not have a treated and AC-determined flare during the RCP were censored at the time of discontinuation.

Table 7. Efficacy Results in Study 2 in IgG4-RD Patients
 | Treatment Group
 | UPLIZNA N = 68 | Placebo N = 67
Time to The First Treated and AC-Determined IgG4-RD Flare (Primary Efficacy Endpoint)
Number of subjects with a IgG4-RD flare | 7 (10.3%) | 40 (59.7%)
Hazard ratio (95% CI) [Based on Cox regression method, with placebo as the reference group.] | 0.13 (0.06, 0.28)
p-value | < 0.0001
Annualized Flare Rate for Treated and AC-Determined IgG4-RD Flares | 0.10 | 0.71
Rate ratio (95% CI) [Estimated from the negative binomial regression, with placebo as the reference group.] | 0.14 (0.06, 0.31)
p-value | < 0.0001
Proportion of Subjects Achieving Treatment-free, Flare-Free Complete Remission at Week 52 [Defined as the lack of evident disease activity (IgG4-RD RI = 0 or investigator's decision) at Week 52, no AC-determined flare during the RCP, and no treatment for flare or disease control except the required 8-week GC taper.] | 39 (57.4%) | 15 (22.4%)
Difference (95% CI) [Based on logistic regression model, with placebo as the reference group.] | 35.0% (19.5%, 50.5%)
p-value | < 0.0001
Proportion of Subjects Achieving Corticosteroid-free, Flare-Free and Complete Remission at Week 52 [Defined as the lack of evident disease activity (IgG4-RD RI = 0 or investigator's decision) at Week 52, no AC-determined flare during the RCP, and no corticosteroid treatment for flare or disease control except the required 8-week GC taper.] | 40 (58.8%) | 15 (22.4%)
Difference (95% CI) | 36.5% (21.0%, 51.9%)
p-value | < 0.0001

For all patients in the trial, the mean (SD) total GC use for IgG4-RD control per patient other than the planned GC taper was lower in the UPLIZNA-treated group compared with the placebo-treated group, with a mean (SD) of 118.25 (438.97) mg prednisone equivalent versus 1384.53 (1723.26) mg prednisone equivalent, respectively during the RCP. Forty-two (62.7%) placebo-treated patients and 7 (10.3%) UPLIZNA-treated patients received GC for IgG4-RD control other than the planned GC taper. The mean (SD) total GC use per patient for the 42 placebo-treated patients was 2202.76 (1709) mg prednisone equivalent and for the 7 UPLIZNA-treated patients was 1148.71 (878) mg prednisone equivalent.

14.3 Generalized Myasthenia Gravis (gMG)

The efficacy of UPLIZNA for the treatment of gMG in adult patients who are anti-acetylcholine receptor (AChR) or anti-muscle specific tyrosine kinase (MuSK) antibody positive was established in Study 3 (NCT04524273), a randomized, double-blind, multicenter, placebo-controlled trial. The randomized, controlled treatment period was 52 weeks for the anti-AChR antibody positive population and 26 weeks for the anti-MuSK antibody positive population. The primary analysis was conducted after week 26 in both populations. UPLIZNA was administered according to the recommended dosage regimen [see Dosage and Administration (2.4)].

Patients met the following eligibility criteria:

- Presence of autoantibodies against AChR or MuSK
- Myasthenia Gravis Foundation of America (MGFA) Clinical Classification Class II to IV
- Myasthenia Gravis-Activities of Daily Living (MG-ADL) score between 6 and 10 with > 50% of this score attributed to non-ocular items or an MG-ADL score ≥ 11
- Quantitative Myasthenia Gravis (QMG) score of ≥ 11
- On a stable dose of a corticosteroid or a specified non-steroidal immunosuppressive therapy, or a combination of both prior to randomization.

In Study 3, a total of 238 patients with gMG were randomized in a 1:1 ratio to receive UPLIZNA or placebo. The majority of patients, 80% (n=190) were anti-AChR antibody positive and 20% (n=48) were anti-MuSK antibody positive.

In the overall study population, 61% of the patients were female. Fifty-three percent of patients were White, 42% were Asian, and 2% were Black or African American. The mean age was 47.5 years (range 18 to 82 years). Mean MG-ADL score at baseline was 9.1 and mean QMG score at baseline was 17.0. At baseline, approximately 79% of patients received acetylcholinesterase inhibitors, 64% of patients received corticosteroids only, 7% of patients received non-steroidal immunosuppressive therapy only, and 29% of patients received corticosteroids and 1 non-steroidal immunosuppressive therapy.

The efficacy of UPLIZNA was measured using MG-ADL scale, which assesses the impact of gMG on daily functions of 8 signs or symptoms that are typically affected in gMG. Each item is assessed on a 4-point scale, where a score of 0 represents normal function and a score of 3 represents loss of ability to perform that function. The total MG-ADL score ranges from 0 to 24, with higher scores indicating more impairment.

The primary efficacy endpoint was the change from baseline in the MG-ADL score at week 26, in the overall population. A statistically significant difference favoring UPLIZNA was observed in the mean change from baseline in MG-ADL total score (−4.2 points in the UPLIZNA-treated group compared to −2.2 points for placebo, difference of −1.9, 95% CI: −2.9, −1.0; p-value < 0.0001).

The secondary endpoint was the change from baseline in the QMG score at week 26 in the overall population. The QMG score is a 13-item categorical grading system that assesses muscle weakness. Each item is assessed on a 4-point scale where a score of 0 represents no weakness and a score of 3 represents severe weakness. A total possible score ranges from 0 to 39, where higher scores indicate more severe impairment.

A statistically significant difference favoring UPLIZNA was observed in the mean change from baseline in QMG total score in the overall population (-4.8 points in the UPLIZNA-treated group compared to -2.3 for placebo, difference -2.5, 95% CI: -3.8, -1.2; p-value = 0.0002).

Secondary endpoints also included change in MG-ADL and QMG scores in the anti-AChR antibody positive and anti-MuSK antibody positive populations.

The results of the primary and secondary endpoints are presented in Table 8, Figure 3, and Figure 4.

Table 8. Change from Baseline in MG-ADL and QMG Total Score at Week 26 in Adult gMG Patients who are Anti-AChR Antibody Positive or Anti-MuSK Antibody Positive (Study 3)
 | Overall Population (Primary) |  | Anti-AChR-Ab+ Population |  | Anti-MuSK-Ab+ Population
 | UPLIZNA N = 119 | Placebo N = 117 | UPLIZNA N = 95 | Placebo N = 93 | UPLIZNA N = 24 | Placebo N = 24
MG-ADL Score
LS Mean | -4.2 | -2.2 | -4.2 | -2.4 | -3.9 | -1.7
Difference | -1.9 |  | -1.8 |  | -2.2
95% CI | (-2.9, -1.0) |  | (-2.9, -0.7) |  | (-4.2, -0.2)
p-value | <0.0001 |  | 0.0015 |  | 0.0297
QMG Score
LS Mean | -4.8 | -2.3 | -4.4 | -2.0 | -5.2 | -3.0
Difference | -2.5 |  | -2.5 |  | -2.3
95% CI | (-3.8, -1.2) |  | (-3.9, -1.0) |  | (-5.3, 0.7)
p-value | 0.0002 |  | 0.0011 |  | NS
Ab+ = antibody positive; CI = confidence interval; LS = least square; NS = not significant

Figure 3. Mean Change from Baseline in MG-ADL Score at Week 26 for Overall Population

Figure 4. Mean Change from Baseline in QMG Score at Week 26 for Overall Population

16 HOW SUPPLIED/STORAGE AND HANDLING

16.1 How Supplied

UPLIZNA (inebilizumab-cdon) injection is a clear to slightly opalescent, colorless to slightly yellow solution supplied as:

- One carton containing three 100 mg/10 mL single-dose vials – NDC 75987-150-03

16.2 Storage and Handling

- Store in a refrigerator at 2°C to 8°C (36°F to 46°F) in original carton to protect from light.
- Do not freeze.
- Do not shake.
- Store vials upright.

17 PATIENT COUNSELING INFORMATION

Advise the patient and/or caregiver to read the FDA-approved patient labeling (Medication Guide).

Infusion Reactions

Inform patients about the signs and symptoms of infusion reactions, including anaphylaxis, and advise them to contact their healthcare provider immediately if they observe signs or symptoms of infusion reactions [see Warnings and Precautions (5.1)].

Infections

Advise patients to contact their healthcare provider for any signs of infection during treatment or after the last dose. Signs include fever, chills, constant cough, or dysuria [see Warnings and Precautions (5.2)].

Advise patients that UPLIZNA may cause reactivation of hepatitis B infection and that monitoring will be required if they are at risk [see Warnings and Precautions (5.2)].

Advise patients that PML has happened with drugs that are similar to UPLIZNA and may happen with UPLIZNA. Inform the patient that PML is characterized by a progression of deficits and usually leads to death or severe disability over weeks or months. Instruct the patient of the importance of contacting their healthcare provider if they develop any symptoms suggestive of PML. Inform the patient that typical symptoms associated with PML are diverse, progress over days to weeks, and include progressive weakness on one side of the body or clumsiness of limbs, disturbance of vision, and changes in thinking, memory, and orientation leading to confusion and personality changes [see Warnings and Precautions (5.2)].

Vaccinations

Advise patients to complete any required vaccinations at least 4 weeks prior to initiation of UPLIZNA. Administration of live-attenuated or live vaccines is not recommended during UPLIZNA treatment and until B-cell recovery [see Warnings and Precautions (5.2)].

Pregnancy

Instruct patients that if they are pregnant or plan to become pregnant while taking UPLIZNA, they should inform their healthcare provider [see Use in Specific Populations (8.1)]. Advise females of reproductive potential that they should use effective contraception during treatment and for 6 months after UPLIZNA therapy [see Use in Specific Populations (8.3)]. Advise patients to register with the UPLIZNA pregnancy exposure registry [see Use in Specific Populations (8.3)].

Manufactured by:
Horizon Therapeutics Ireland DAC
Dublin, Ireland U.S. License No. 2022
Patent: http://pat.amgen.com/uplizna/
©2025 Amgen Inc. All rights reserved.
1-800-772-6436

1XXXXXX-V5

Medication Guide
UPLIZNA® (up-liz'-nah)
(inebilizumab-cdon)
injection, for intravenous use

What is the most important information I should know about UPLIZNA?
UPLIZNA may cause serious side effects, including:
Infusion reactions. UPLIZNA can cause infusion reactions, including anaphylaxis, that can be serious or may cause you to be hospitalized. You will be monitored during your infusion and for at least 1 hour after each infusion of UPLIZNA for signs and symptoms of an infusion reaction. Tell your healthcare provider right away if you get any of these symptoms:

- headache
- nausea

- sleepiness
- shortness of breath

- fever
- muscle aches

- rash
- palpitations

If you develop an infusion reaction, your healthcare provider may need to stop or slow down the rate of your infusion and treat your symptoms.

Infections. Infections can happen during treatment with UPLIZNA. Tell your healthcare provider right away if you have an infection or get any of these symptoms:

- painful and frequent urination

- nasal congestion, runny nose, sore throat, fever, chills, cough, body aches

- UPLIZNA taken before or after other medicines that weaken the immune system may increase your risk of getting infections.
- Hepatitis B virus (HBV) reactivation. Before starting treatment with UPLIZNA, your healthcare provider will do blood tests to check for hepatitis B viral infection. If you have ever had hepatitis B virus infection, the hepatitis B virus may become active again during or after treatment with UPLIZNA. Hepatitis B virus becoming active again (called reactivation) may cause serious liver problems, including liver failure or death. Your healthcare provider will monitor you if you are at risk for hepatitis B virus reactivation during treatment and after you stop receiving UPLIZNA.
- Progressive Multifocal Leukoencephalopathy (PML). PML may happen with UPLIZNA. PML is a rare brain infection that leads to death or severe disability. Symptoms of PML may get worse over days to weeks. Call your healthcare provider right away if you get any of these symptoms:

- weakness on one side of the body
- loss of coordination in your arms and legs

- changes in your vision
- changes in thinking or memory

- confusion
- changes in your personality

- Tuberculosis (TB). TB is caused by an infection in the lungs. Before starting treatment with UPLIZNA, your healthcare provider will check to see if you are at risk for getting TB or have ever had TB.
- Vaccinations. Certain vaccines, called "live" or "live attenuated" vaccines, are not recommended in people receiving UPLIZNA. Talk to your healthcare provider before receiving any vaccinations. If you have a baby and you were receiving UPLIZNA during pregnancy, it is important to tell your baby's healthcare provider about your UPLIZNA use so they can decide when your baby should receive any vaccine.

See "What are the possible side effects of UPLIZNA?" for more information about side effects.

What is UPLIZNA?

- UPLIZNA is a prescription medicine used to treat adults with:
  - Neuromyelitis optic spectrum disorder (NMOSD) who are anti-aquaporin-4 (AQP4) antibody positive.
  - Immunoglobulin G4-related disease (IgG4-RD).
  - Generalized myasthenia gravis (gMG) who are anti-acetylcholine receptor (AChR) or anti-muscle specific tyrosine kinase (MuSK) antibody positive.
- It is not known if UPLIZNA is safe or effective in children.

Who should not receive UPLIZNA?
You should not receive UPLIZNA if you have:

- had a life-threatening infusion reaction to UPLIZNA.
- an active hepatitis B virus infection.
- active or untreated inactive (latent) tuberculosis.

Before receiving UPLIZNA, tell your healthcare provider about all of your medical conditions, including if you:

- have or think you have an infection.
- have ever taken, currently take, or plan to take medicines that affect your immune system, or other treatments for NMOSD, IgG4-RD, or gMG. These medicines may increase your risk of getting an infection.
- have or have ever had hepatitis B or are a carrier of the hepatitis B virus.
- have or have ever had tuberculosis.
- have had a recent vaccination or are scheduled to receive any vaccinations. You should receive any required vaccines at least 4 weeks before you start treatment with UPLIZNA.
- are pregnant or plan to become pregnant. It is not known if UPLIZNA will harm your unborn baby. Females should use birth control (contraception) during treatment with UPLIZNA and for 6 months after your last infusion of UPLIZNA.
- Pregnancy Exposure Registry: There is a pregnancy registry to collect information about women who are exposed to UPLIZNA during pregnancy. The purpose of this registry is to collect information about the health of you and your baby. If you become pregnant while taking UPLIZNA, you are encouraged to enroll in the pregnancy registry by calling 1-303-724-4644 or by visiting online at www.upliznapregnancyregistry.com.
- are breastfeeding or plan to breastfeed. It is not known if UPLIZNA passes into your breast milk. Talk to your healthcare provider about the best way to feed your baby if you receive UPLIZNA.

Tell your healthcare provider about all the medicines you take, including prescription and over-the-counter medicines, vitamins, and herbal supplements.

How will I receive UPLIZNA?

- UPLIZNA is given through a needle placed in a vein (IV or intravenous infusion) in your arm.
- Before treatment with UPLIZNA, your healthcare provider will give you a corticosteroid medicine, an antihistamine, and a fever prevention medicine to help infusion reactions become less frequent and less severe. See "What is the most important information I should know about UPLIZNA?"
- Your first dose of UPLIZNA will be given as 2 separate infusions, 2 weeks apart.
- Your next doses of UPLIZNA will be given as one infusion every 6 months.
- Each infusion will last about 1 hour and 30 minutes. After each infusion, you will be monitored by a healthcare provider for at least 1 hour.

What are the possible side effects of UPLIZNA?
UPLIZNA may cause serious side effects, including:

- See "What is the most important information I should know about UPLIZNA?"
- low blood cell counts. UPLIZNA may cause a decrease in some types of blood cells. Your healthcare provider will do blood tests to check your blood cell counts.

The most common side effects in patients with NMOSD include urinary tract infection and joint pain.
The most common side effects in patients with IgG4-RD include urinary tract infection and low white blood cell count.
The most common side effects in patients with gMG include headache and infusion-related reactions.
These are not all the possible side effects of UPLIZNA.
Call your doctor for medical advice about side effects. You may report side effects to FDA at 1-800-FDA-1088.

General information about the safe and effective use of UPLIZNA.
Medicines are sometimes prescribed for purposes other than those listed in a Medication Guide. You can ask your pharmacist or healthcare provider for information about UPLIZNA that is written for health professionals.

What are the ingredients in UPLIZNA?
Active ingredient: inebilizumab-cdon.
Inactive ingredients: L-histidine, L-histidine hydrochloride monohydrate, polysorbate 80, sodium chloride, α,α-trehalose dihydrate, and water for injection.

AMGEN
Manufactured by: Horizon Therapeutics Ireland DAC.,
Dublin, Ireland U.S. License No. 2022
Patent: http://pat.amgen.com/uplizna/
©2020, 2025 Horizon Therapeutics Ireland DAC All rights reserved.
1-800-772-6436

This Medication Guide has been approved by the U.S. Food and Drug Administration

Revised: 12/2025

PRINCIPAL DISPLAY PANEL - 100 mg/10 mL Vial Label

NDC 75987-150-01

UPLIZNA®
inebilizumab-cdon

Injection

100 mg/10 mL (10mg/mL)

FOR INTRAVENOUS INFUSION
AFTER DILUTION

PL1882Y
Rx Only

PRINCIPAL DISPLAY PANEL - 100 mg/10 mL Vial Carton

UPLIZNA®
inebilizumab-cdon
Injection

100 mg/10 mL (10mg/mL)

FOR INTRAVENOUS INFUSION
AFTER DILUTION

Must dilute product before use

Prepare 3 single-dose vials for complete dose of 300 mg
Discard any unused portion

Contents: 3 single-dose vials

Rx Only

NDC 75987-150-03

Attention Pharmacist:
Dispense the accompanying
Medication Guide
to each patient.

AMGEN

🠅 STORE VIALS UPRIGHT 🠅